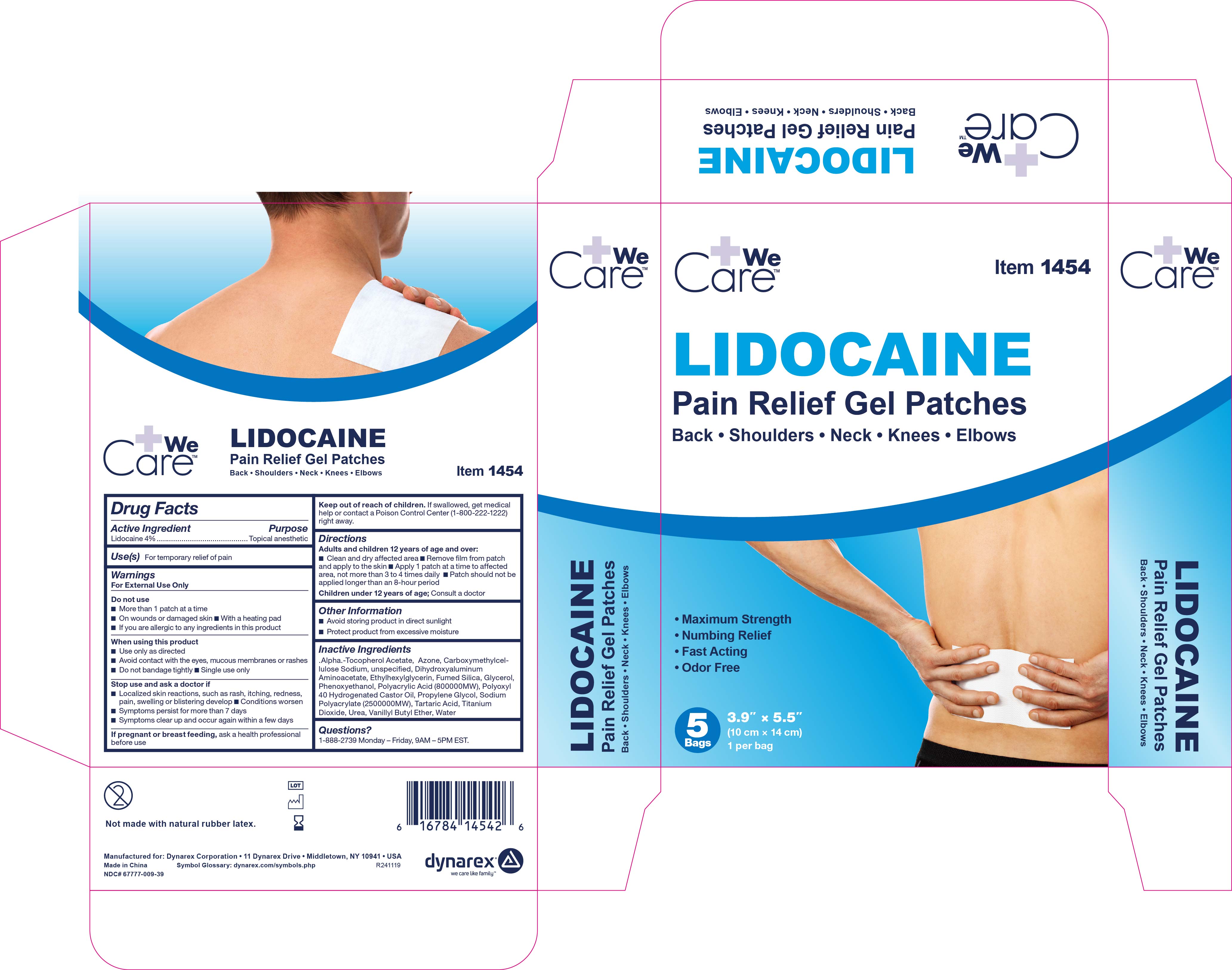 DRUG LABEL: Lidocaine Pain Relief Gel Patch
NDC: 67777-009 | Form: PATCH
Manufacturer: Dynarex
Category: otc | Type: HUMAN OTC DRUG LABEL
Date: 20260128

ACTIVE INGREDIENTS: LIDOCAINE 4 mg/100 mg
INACTIVE INGREDIENTS: SILICON DIOXIDE; UREA; POLYACRYLIC ACID (800000 MW); CARBOXYMETHYLCELLULOSE SODIUM, UNSPECIFIED; TITANIUM DIOXIDE; ETHYLHEXYLGLYCERIN; PEG-40 HYDROGENATED CASTOR OIL; .ALPHA.-TOCOPHEROL ACETATE; SODIUM POLYACRYLATE (2500000 MW); PROPYLENE GLYCOL; DIHYDROXYALUMINUM AMINOACETATE; GLYCERIN; PHENOXYETHANOL; TARTARIC ACID; WATER; VANILLYL BUTYL ETHER; LAUROCAPRAM

1454 Lidocaine Pain Relief Gel-Patch NDC 67777-009-40

Active Ingredients

Lidocaine 4%

Puropose

Topical Anesthetic

Use

For temporary relief of pain

Warnings

For External Use Only

Do not use

- more than 1 patch at a time
- on wounds or damaged skin
- with a heating pad
- if you are allergic to any ingredients of this product

When using this product

- Use only as directed
- Avoid contact with the eyes, mucous membranes or rashes
- Do not bandage tightly
- Single use only

Stop use and ask a doctor if

- Localized skin reactions, such as rash, itching, redness, pain, swelling and blistering develop
- Conditions worsen
- Symptoms persist for more than 7 days
- Symptoms clear up and occur again within a few days

if pregnant or breast feeding

Ask a health professional before use

Keep out of reach of children.

If swallowed, get medical help or contact a Poison Control Center (1-800-222-1222) right away.

Directions

Adults and children 12 years of age and over:

- Clean and dry affected area
- Remove film from patch and apply to the skin
- Apply 1 patch at a time to affected area, not more than 3 to 4 times daily
- Patch should not be applied longer than an 8 hour period

Children under 12 years of age: Consult a doctor

Other Information

- Avoid storing product in direct sunlight
- Protect product from excessive moisture

Inactive Ingredients

.

.Alpha.-Tocopherol Acetate, Azone, Carboxymethylcellulose Sodium , unspecified, Dihydroxyaluminum Aminoacetate, Ethylhexylglycerin, Fumed Silica, Glycerol, Phenoxyethanol, Polyacrylic Acid (800000MW), Polyoxyl 40 Hydrogenated Castor Oil, Propylene Glycol, Sodium Polyacrylate (2500000 MW), Tartaric Acid, Titanium Dioxide, Urea, Vanillyl Butyl Ether, Water

Questions?

1-888-DYNAREX

Label

Lidocaine Pain Relief Patch